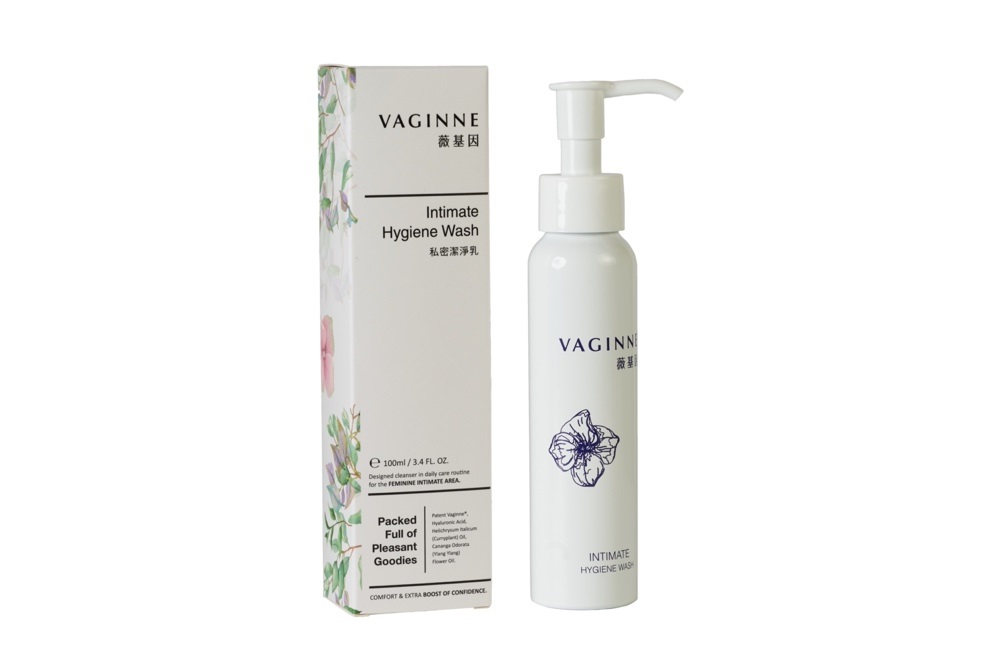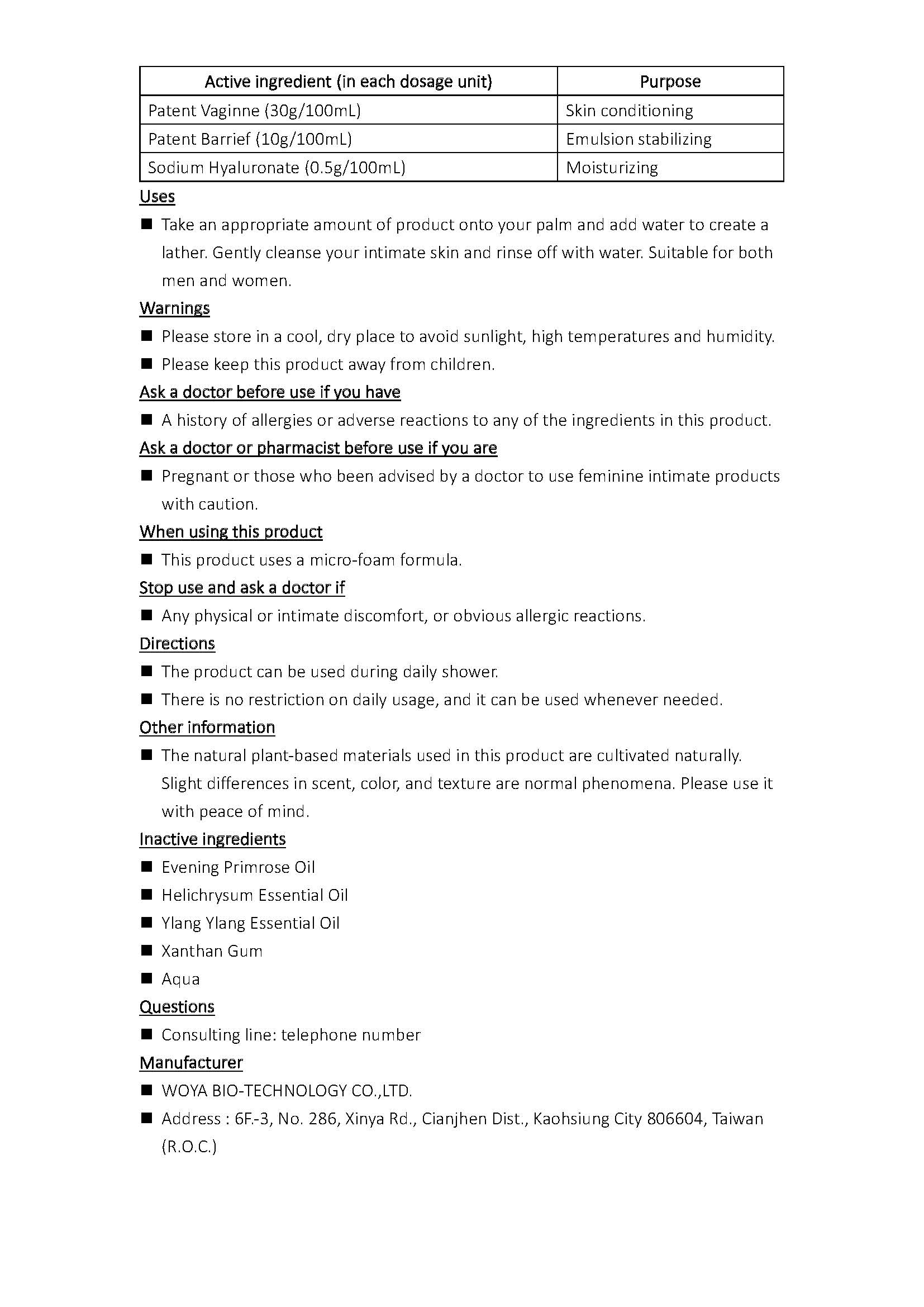 DRUG LABEL: Vaginne Intimate Hygiene Wash
NDC: 83500-001 | Form: GEL
Manufacturer: WOYA BIO-TECHNOLOGY CO.,LTD.
Category: otc | Type: HUMAN OTC DRUG LABEL
Date: 20230526

ACTIVE INGREDIENTS: HYALURONATE SODIUM 0.5 g/100 mL; LACTIC ACID 30 g/100 mL; SORBITAN MONOLAURATE 10 g/100 mL
INACTIVE INGREDIENTS: XANTHAN GUM; EVENING PRIMROSE OIL; YLANG-YLANG OIL; HELICHRYSUM ITALICUM FLOWER OIL; WATER

Active ingredient (in each dosage unit) | Purpose
Patent Vaginne (30g/100mL) | Skin conditioning
Patent Barrief (10g/100mL) | Emulsion stabilizing
Sodium Hyaluronate (0.5g/100mL) | Moisturizing

Uses

Take an appropriate amount of product onto your palm and add water to create a lather. Gently cleanse your intimate skin and rinse off with water. Suitable for both men and women.

Warnings

Please store in a cool, dry place to avoid sunlight, high temperatures and humidity.
Please keep this product away from children.

Ask a doctor before use if you have

A history of allergies or adverse reactions to any of the ingredients in this product.

Ask a doctor or pharmacist before use if you are

Pregnant or those who been advised by a doctor to use feminine intimate products with caution.

When using this product

This product uses a micro-foam formula.

Stop use and ask a doctor if

Any physical or intimate discomfort, or obvious allergic reactions.

Directions

The product can be used during daily shower.

There is no restriction on daily usage, and it can be used whenever needed.

Other information

The natural plant-based materials used in this product are cultivated naturally. Slight differences in scent, color, and texture are normal phenomena. Please use it with peace of mind.

Inactive ingredients

Evening Primrose Oil
Helichrysum Essential Oil
Ylang Ylang Essential Oil
Xanthan Gum
Aqua

Uses

Take an appropriate amount of product onto your palm and add water to create a lather. Gently cleanse your intimate skin and rinse off with water. Suitable for both men and women.

Warnings

Please store in a cool, dry place to avoid sunlight, high temperatures and humidity.

Please keep this product away from children.

Directions

The product can be used during daily shower.
There is no restriction on daily usage, and it can be used whenever needed.

Purpose

Skin conditioning

Emulsion stabilizing

Moisturizing

Vaginne® Intimate Hygiene Wash